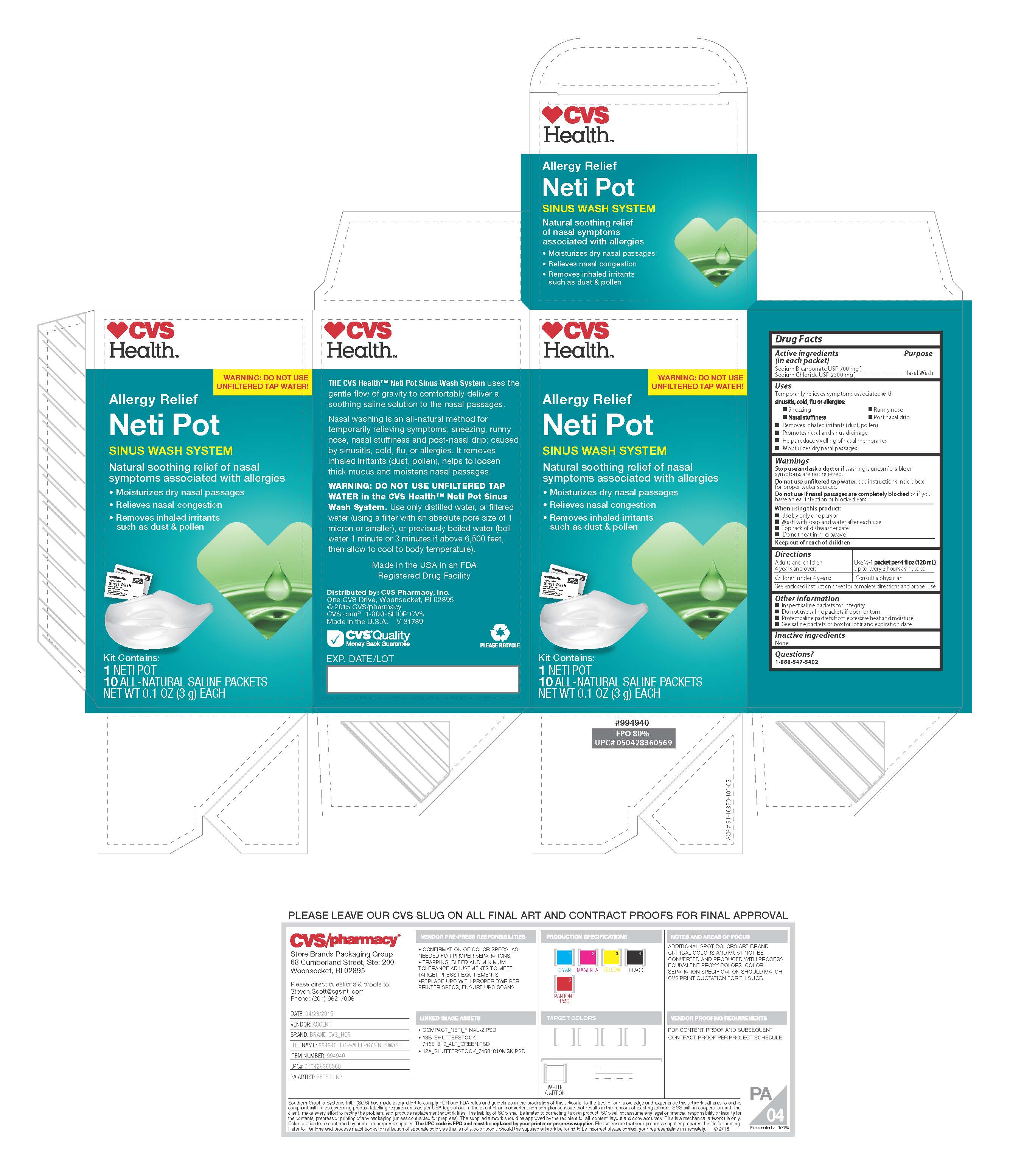 DRUG LABEL: CVS
NDC: 69842-349 | Form: KIT | Route: NASAL
Manufacturer: CVS Pharmacy, Inc.
Category: otc | Type: HUMAN OTC DRUG LABEL
Date: 20250203

ACTIVE INGREDIENTS: SODIUM BICARBONATE 22.8 mg/100 mg; SODIUM CHLORIDE 77.8 mg/100 mg
INACTIVE INGREDIENTS: WATER

CVS- Allergy relief Netipot

Active ingredients

(in each packet)

Sodium Bicarbonate USP 700 mg

Sodium Chloride USP 2300 mg

Purpose

Nasal Wash

Uses

Temporarily relieves symptoms associated with

sinusitis, cold, flu or allergies:

-Sneezing

-Runny nose

-Nasal stuffiness

-Post nasal drip

-Removes inhaled irritants (dust, pollen)

-Promotes nasal and sinus drainage

-Helps reduce swelling of nasal membranes

-Moisturizes dry nasal passages

Warnings

Stop use and ask a doctor if washing is uncomfortable or

symptoms are not reduced.

Do not use unfiltered tap water. See instructions inside box

for proper water sources.

Do not use if nasal passages are completely blocked or if you

have an ear infection or blocked ears.

When using this product:

- Use by only one person
- Wash with soap and water after each use
- Top rack of dishwasher safe
- Do not heat in microwave

Keep out of reach of children

Directions:

Adults and children 4 years and over: use 1/2 - 1 packet per 4 fl. oz (120 mL) up to every 2 hours as needed

Children under 4 years: Consult a physician

See enclosed instruction sheet for complete instructions and proper use

Other information

- Inspect saline packets for integrity
- Do not use saline packets if open or torn
- Protect saline packets from excessive heat and moisture
- See saline packets or box for lot number and expiration date

Inactive ingredients: none

Questions?

1-888-547-5492

INSTRUCTIONS FOR USE

*IMPORTANT NOTE
Do not sinus wash with unfiltered tap water. Use either distilled, or sterile, or filtered (using a filter with an absolute pore size of 1 micron orsmaller) or previously boiled water (boil water 1 minute or 3 minutes if at elevations above 6,500 feet then allow to cool to bodytemperature).

Sinus Wash Compact Neti Pot Instructions
Read through entire instruction
sheet before using for the first time.

DO NOT SINUS WASH
WITH UNFILTERED TAP WATER.
See important note* for proper water sources.

Warning: Do not rinse if nasal passages are completely blocked or if you have an ear infection or blocked ears.

Should I use an Isotonic or Hypertonic Solution?

Any Sinus Wash Device can be used with the enclosed Saline packets to make either an Isotonic or Hypertonic solution. Check with the guide below or consult with your physician for best use.

Isotonic Solution 1/2 Saline Packet per 4 fl oz. (120 mL)

Hypertonic Solution 1 Saline Packets per 4 fl oz. (120 mL)

An Isotonic solution creates a mild, less concentrated salt solution of 9 mg of Sodium Chloride per mL of water, which has a similar salt concentration of your body and may be more comfortable to use for some people initially than a more concentrated Hypertonic solution.

A Hypertonic solution creates a higher, more concentrated salt solution which is similar to the salt content of ocean water.

What is the Sinus Wash System?
The Sinus Wash System is an all natural and medically proven method for relieving allergies, nasal congestion, discomfort caused by dry air, sinus infections, rhinitis of pregnancy and
soothing irritated nasal passages. It gently washes away mucus buildup from the nose and improves breathing.
Because it is gentle, the system can be used up to every 2 hours as needed. Some people use it as routinely as they brush their teeth while others use it only on days when they need it.

ACP No. 99-40330-205-00

Instructions for Use of the Compact Neti Pot:
Directions & Dosage: Read through entire section before using for the first time.

1. Pour the pre-mixed saline dry ingredients into the Compact Neti Pot. First-time users should start with 1/2 packet of the saline dry
ingredients. As you become more accustomed to the system, work up to using 1 full packet. Additional packets may be purchased from your nearest pharmacy.

2. Fill the pot to the 4 oz. line with proper water*. This makes 1/2 cup (4 oz.) of solution.

3. Stir thoroughly until the dry ingredients have completely dissolved.

4. Proper head position allows solution to flow through the nose by gravity.

•Lean over the sink with your head bent down so you are looking directly into the basin. Holding the Neti Pot in your right hand, gently insert the spout into your right nostril so that it forms a comfortable seal.

• Rotate your head so that the right nostril is directly above the left. The forehead should remain higher than the chin. Raise the Neti Pot so that the solution enters the right nostril. In a few moments, the solution will begin to drain out the left nostril into the sink. Do not inhale
or “snort” solution into the nose – breathe through your mouth.

5. When the Neti Pot is empty, exhale through both nostrils to clear them of excess mucus and solution. Gently blow your nose into a tissue.

6. Repeat the procedure on the left nostril.

7. Thoroughly rinse the Neti Pot after each use with water that has been distilled, sterilized, filtered or previously boiled and leave the pot open to air dry completely. The Compact Neti Pot is top-rack dishwasher safe.

Hints for a more comfortable nasal wash:
• Begin using the Sinus Wash System slowly – especially with children. A full pot of solution on each side is not necessary to receive the full benefit.
• If the solution is too warm or too cold, the nasal wash will be uncomfortable.
• If stinging or irritation occurs, try using 1/2 packet of dry ingredients per pot. Gradually work up to using the
solution at full strength using 1 full packet per pot. Do not use less than 1/2 packet.
• If you experience ear discomfort after use, try to blow your nose more gently after the wash. If the problem persists, the openings of your Eustachian tubes may be particularly wide and use of the system should be discontinued.
• Breathe continuously through the mouth when using the Sinus Wash System to avoid solution draining from the back of the nose into the mouth.
• Some people experience irritation of the skin just inside the nostrils with repeated nasal washing. Applying a thin layer of aloe to the inside of the nostrils before or after the nasal wash will be soothing.